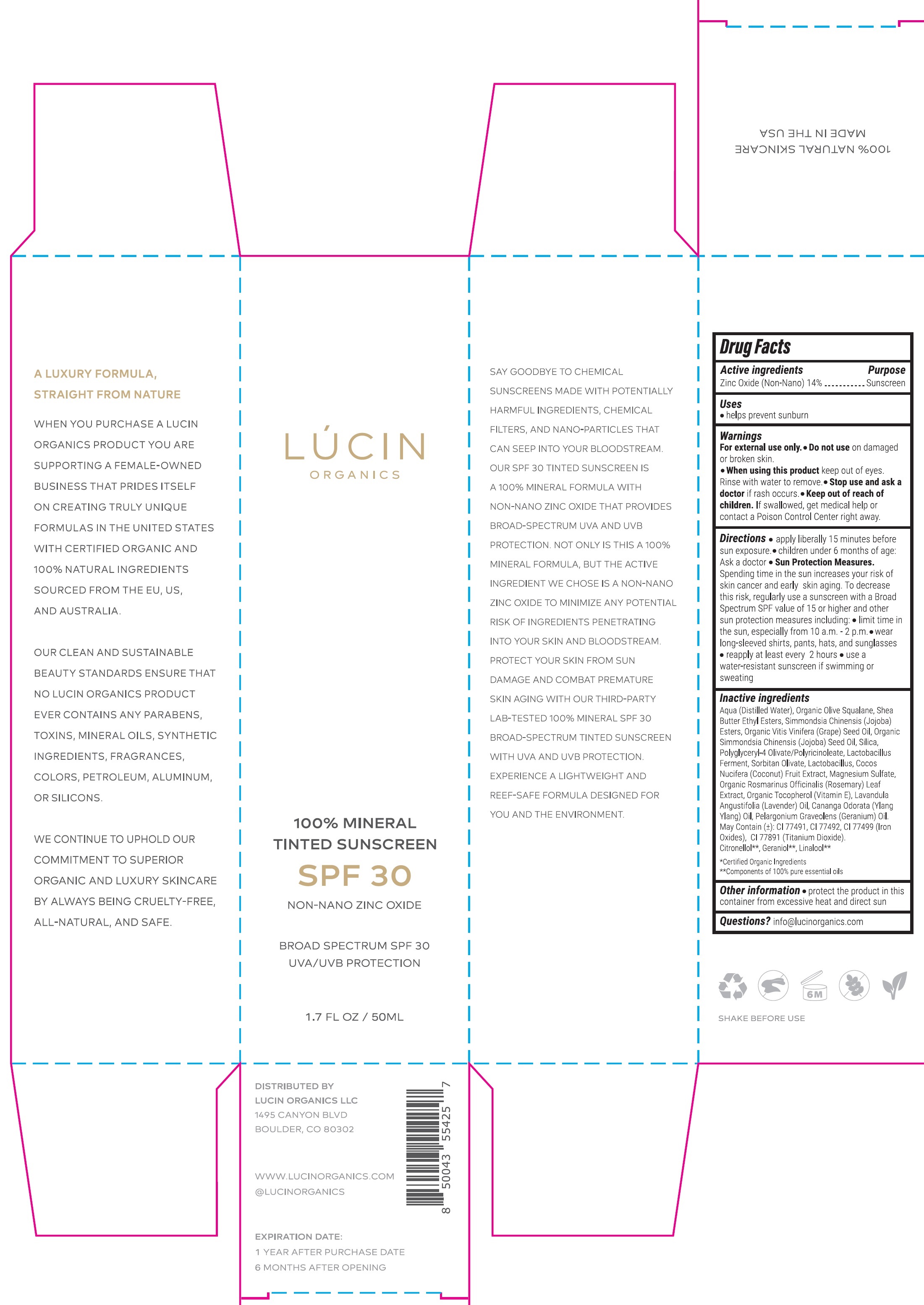 DRUG LABEL: Lucin Organics Tinted Sunscreen SPF 30 Non Nano Zinc Oxide
NDC: 84124-000 | Form: CREAM
Manufacturer: Lucin Organics, LLC
Category: otc | Type: HUMAN OTC DRUG LABEL
Date: 20240304

ACTIVE INGREDIENTS: ZINC OXIDE 140 mg/1 mL
INACTIVE INGREDIENTS: WATER; SHEA BUTTER ETHYL ESTERS; GRAPE; SILICON DIOXIDE; POLYGLYCERYL-4 OLIVATE/POLYRICINOLEATE; SORBITAN OLIVATE; BIFIDOBACTERIUM ANIMALIS LACTIS; COCONUT; MAGNESIUM SULFATE, UNSPECIFIED FORM; ROSEMARY; .ALPHA.-TOCOPHEROL; LAVENDER OIL; GERANIUM OIL, ALGERIAN TYPE

Lucin Organics Tinted Sunscreen SPF 30 Non Nano Zinc Oxide

Active ingredients

Zinc Oxide (Non-Nano) 14%

Purpose

Sunscreen

Uses

- helps prevent sunburn

Warnings

For external use only.

• Do not use

on damaged or broken skin.

• When using this product

keep out of eyes. Rinse with water to remove.

• Stop use and ask a doctor

if rash occurs.

• Keep out of reach of children.

If swallowed, get medical help or contact a Poison Control Center right away.

Directions

• apply liberally 15 minutes before sun exposure. • children under 6 months of age: Ask a doctor • Sun Protection Measures. Spending time in the sun increases your risk of skin cancer and early skin aging. To decrease this risk, regularly use a sunscreen with a Broad Spectrum SPF value of 15 or higher and other sun protection measures including: • limit time in the sun, especially from 10 a.m. - 2 p.m. • wear long-sleeved shirts, pants, hats, and sunglasses • reapply at least every 2 hours • use a water-resistant sunscreen if swimming or sweating

Inactive ingredients

Aqua (Distilled Water), Organic Olive Squalane, Shea Butter Ethyl Esters, Simmondsia Chinensis (Jojoba) Esters, Organic Vitis Vinifera (Grape) Seed Oil, Organic Simmondsia Chinensis (Jojoba) Seed Oil, Silica, Polyglyceryl-4 Olivate/Polyricinoleate, Lactobacillus Ferment, Sorbitan Olivate, Lactobacillus, Cocos Nucifera (Coconut) Fruit Extract, Magnesium Sulfate, Organic Rosmarinus Officinalis (Rosemary) Leaf Extract, Organic Tocopherol (Vitamin E), Lavandula Angustifolia (Lavender) Oil, Cananga Odorata (Ylang Ylang) Oil, Pelargonium Graveolens (Geranium) Oil. May Contain (±): CI 77491, CI 77492, CI 77499 (Iron Oxides), CI 77891 (Titanium Dioxide). Citronellol**, Geraniol**, Linalool**

*Cerified Oraganic Ingredients

** Components of 100% pure essential oils

Other information

- protect the product in this container from excessive heat and direct sun

Questions?

info@lucinorganics.com